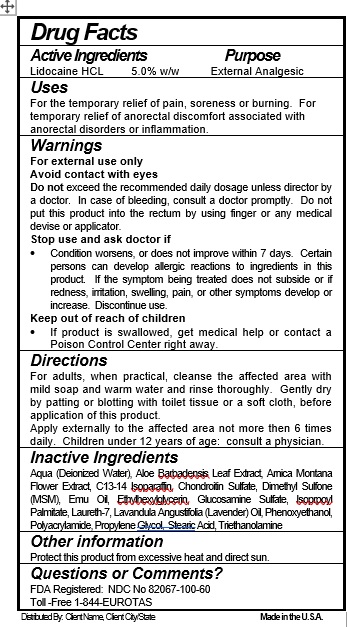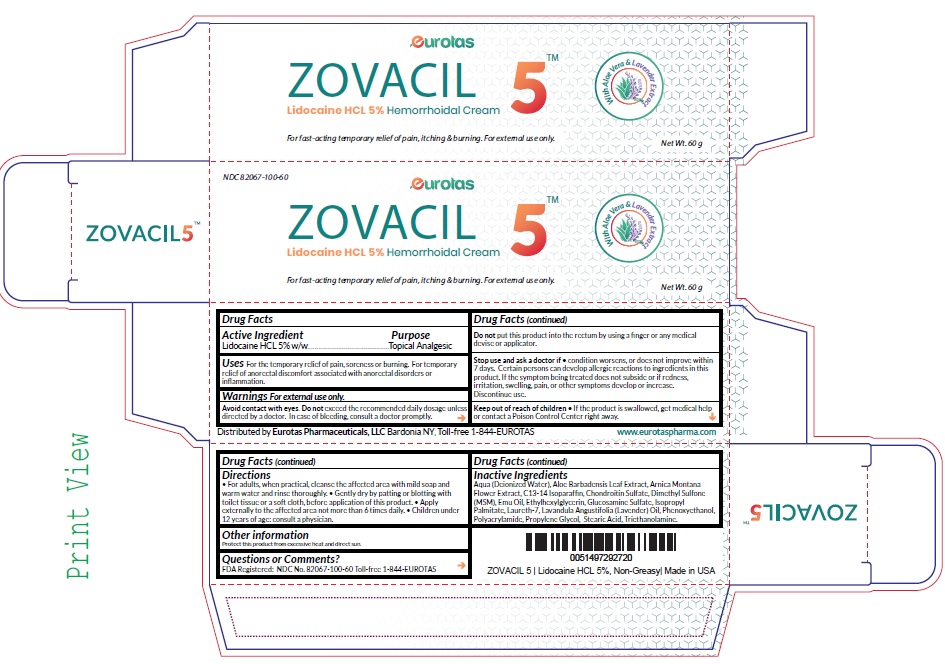 DRUG LABEL: Zovacil 5
NDC: 82067-100 | Form: CREAM
Manufacturer: EUROTAS PHARMACEUTICALS, LLC
Category: otc | Type: HUMAN OTC DRUG LABEL
Date: 20220629

ACTIVE INGREDIENTS: LIDOCAINE 5 g/100 g
INACTIVE INGREDIENTS: ALOE VERA LEAF; WATER; ARNICA MONTANA FLOWER; C13-14 ISOPARAFFIN; CHONDROITIN 6-SULFATE; DIMETHYL SULFONE; EMU OIL; ETHYLHEXYLGLYCERIN; GLUCOSAMINE SULFATE; ISOPROPYL PALMITATE; LAVANDULA ANGUSTIFOLIA SUBSP. ANGUSTIFOLIA FLOWER; PHENOXYETHANOL; POLYACRYLAMIDE (10000 MW); PROPYLENE GLYCOL; STEARIC ACID; TRIETHANOLAMINE BENZOATE; LAURETH-7

Drug Facts

Active Ingredient

Lidocaine HCL 5.0% w/w

Purpose

External Analgesic

Uses

For the temporary relief of pain, soreness or burning. For temporary relief of anorectal discomfort associated with anorectal disorders or inflammation.

Warnings

For external use only
Avoid contact with eyes
Do not exceed the recommended daily dosage unless director by a doctor. In case of bleeding, consult a doctor promptly. Do not put this product into the rectum by using a finger or any medical device or applicator.
Stop use and ask doctor if
• Condition worsens, or does not improve within 7 days. Certain persons can develop allergic reactions to ingredients in this product. If the symptom being treated does not subside or if redness, irritation, swelling, pain, or other symptoms develop or increase. Discontinue use.
Keep out of reach of children
• If a product is swallowed, get medical help or contact a Poison Control Center right away.

Directions

For adults, when practical, cleanse the affected area with mild soap and warm water and rinse thoroughly. Gently dry by patting or blotting with toilet tissue or a soft cloth, before application of this product.
Apply externally to the affected area not more than 6 times daily. Children under 12 years of age: consult a physician.

Inactive Ingredients

Aqua (Deionized Water), Aloe Barbadensis Leaf Extract, Arnica Montana Flower Extract, C13-14 Isoparaffin, Chondroitin Sulfate, Dimethyl Sulfone (MSM), Emu Oil, Ethylhexylglycerin, Glucosamine Sulfate, Isoprpoyl Palmitate, Laureth-7, Lavandula Angustifolia (Lavender) Oil, Phenoxyethanol, Polyacrylamide, Propylene Glycol, Stearic Acid, Triethanolamine

Other information

Protect this product from excessive heat and direct sun.

Questions or Comments?

FDA Registered: NDC No 82067-100-60
Toll -Free 1-844-EUROTAS